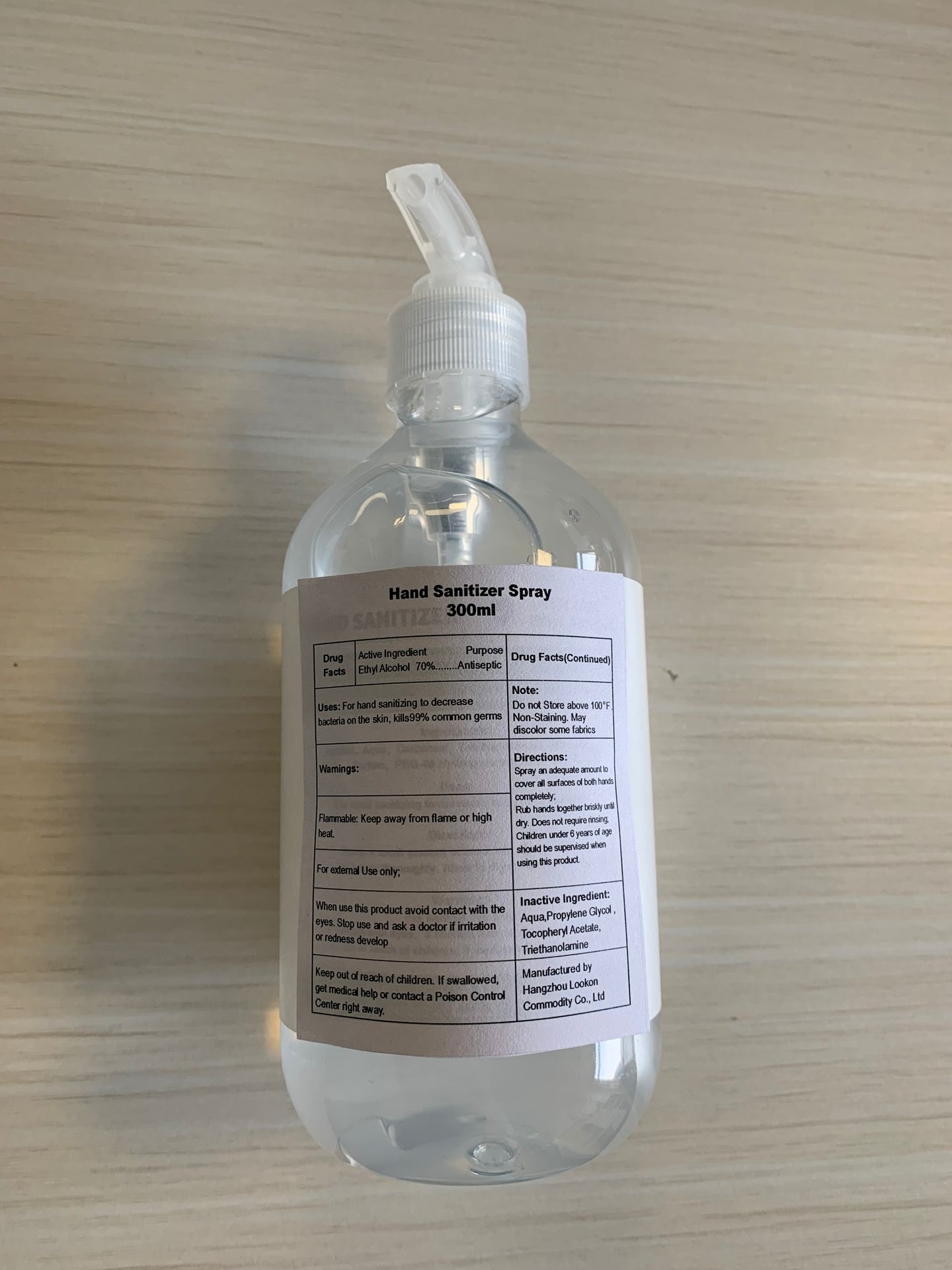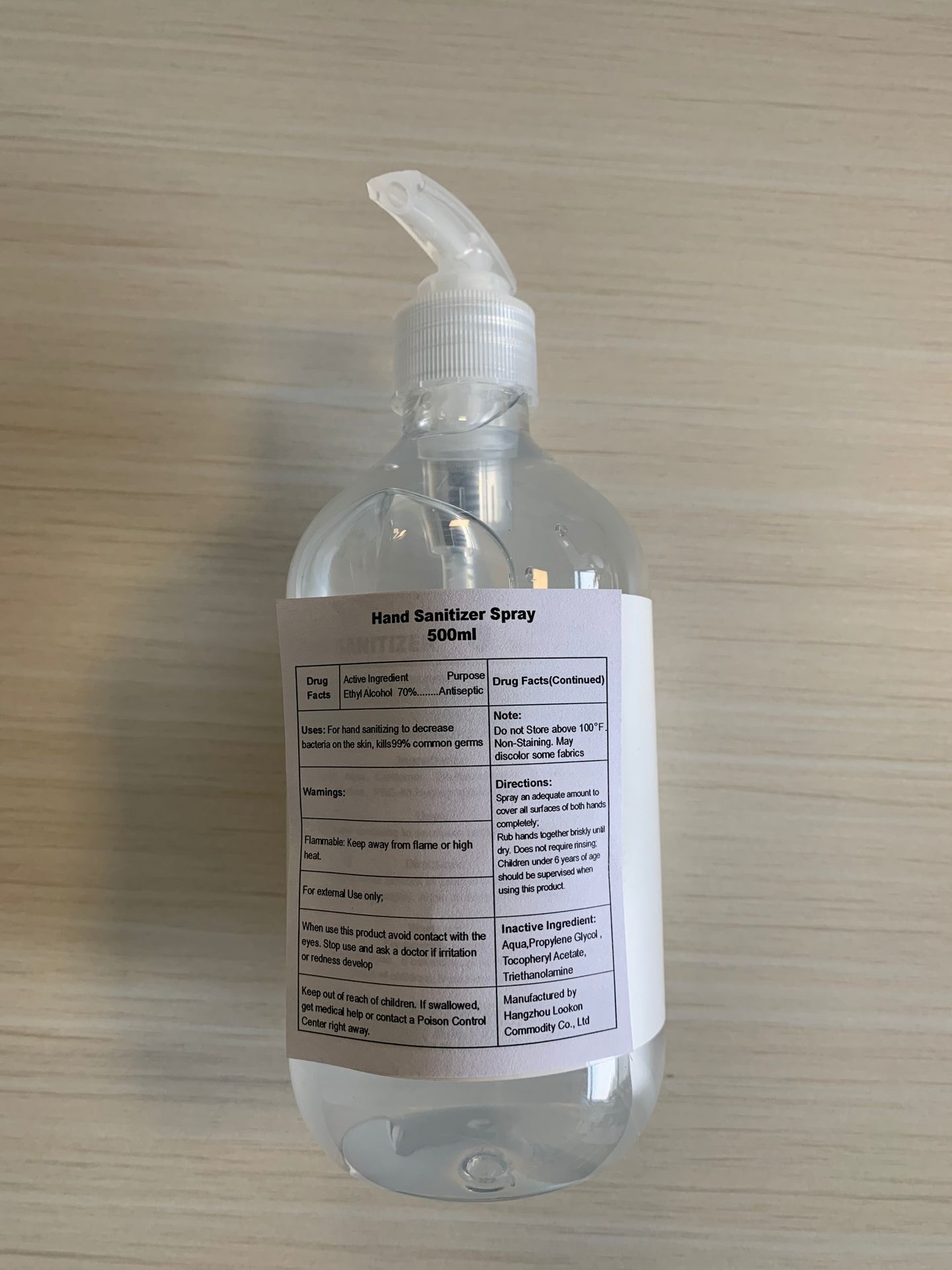 DRUG LABEL: Hand Sanitizer
NDC: 74835-003 | Form: SPRAY
Manufacturer: Hangzhou Lookon Commodity Co., Ltd
Category: otc | Type: HUMAN OTC DRUG LABEL
Date: 20201213

ACTIVE INGREDIENTS: ALCOHOL 70 mL/100 mL
INACTIVE INGREDIENTS: .ALPHA.-TOCOPHEROL ACETATE, D-; TROLAMINE; WATER; PROPYLENE GLYCOL

Hand Sanitizer Spray

Active Ingredient

Ethyl Alcohol 70%

Purpose

Antiseptic

Uses

For hand sanitizing to decrease bacteria on the skin, kills 99% common germs

Warnings

Flammable: Keep away from flame or high heat.

For external Use only;

When use

When use this product avoid contact with the eyes.

Stop use

Stop use and ask a doctor if irritation or redness develop

Keep out of reach of children. If swallowed,get medical help or contact a Poison Control Center right away.

Note

Do not Store above 100 . Non-Staining. May discolor some fabrics.

Directions

Spray an adequate amount to cover all surfaces of both hands completely;

Rub hands together briskly until dry. Does not require rinsing;

Children under 6 years of age should be supervised when using this product.

Inactive Ingredient

Aqua,Propylene Glycol ,Tocopheryl Acetate,Triethanolamine

Package Label

Hand Sanitizer Spray

300ml

NDC: 74835-003-01

Package Label

Hand Sanitizer Spray

500ml

NDC: 74835-003-02